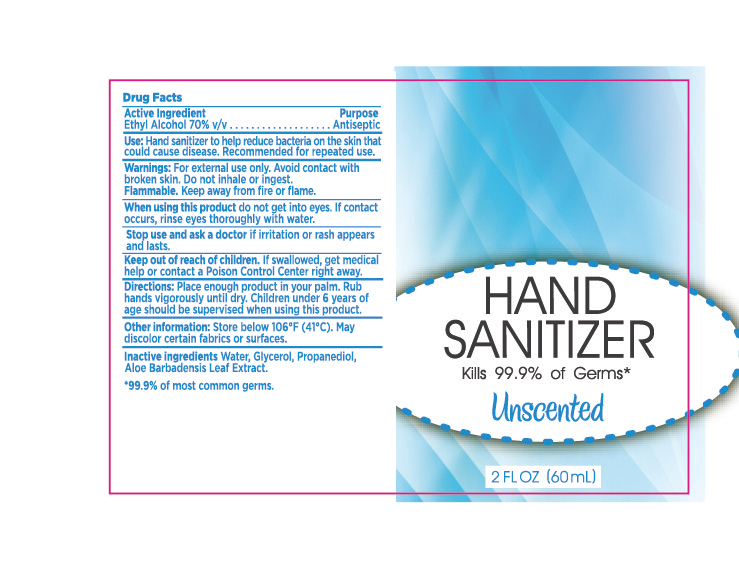 DRUG LABEL: HAND SANITIZER
NDC: 47993-286 | Form: GEL
Manufacturer: NINGBO JIANGBEI OCEAN STAR TRADING CO.,LTD
Category: otc | Type: HUMAN OTC DRUG LABEL
Date: 20201105

ACTIVE INGREDIENTS: ALCOHOL 70 mL/100 mL
INACTIVE INGREDIENTS: WATER; GLYCERIN; PROPANEDIOL; ALOE VERA LEAF

47993-286

Active ingredients

Ethyl Alcohol 70% V/V

PURPOSE

Antiseptic

Uses：

Hand sanitizer to help reduce bacteria on the skin that could cause disease. Recommended for repeated use.

Warnings:

For external use only. Avoid contact with broken skin. Do not inhale or ingest.

Flammable. Keep away from fire or flame.

When using this product do not get into eyes. If contact occurs, rinse eyes thoroughly with water.

Stop use and ask a doctor if irritation or rash appears and lasts.

Keep out of reach of children. If swallowed, get medical help or contact a Poison Control Center right away.

Directions:

Place enough product in your palm. Rub hands vigorously until dry. Children under 6 years of age should be supervised when using this product.

Other information：

Store below 106℉(41℃). May discolor certain fabrics or surfaces.

Inactive Ingredients:

Water,Glycerol,Propanediol,Aloe Barbadensis Leaf Extract.